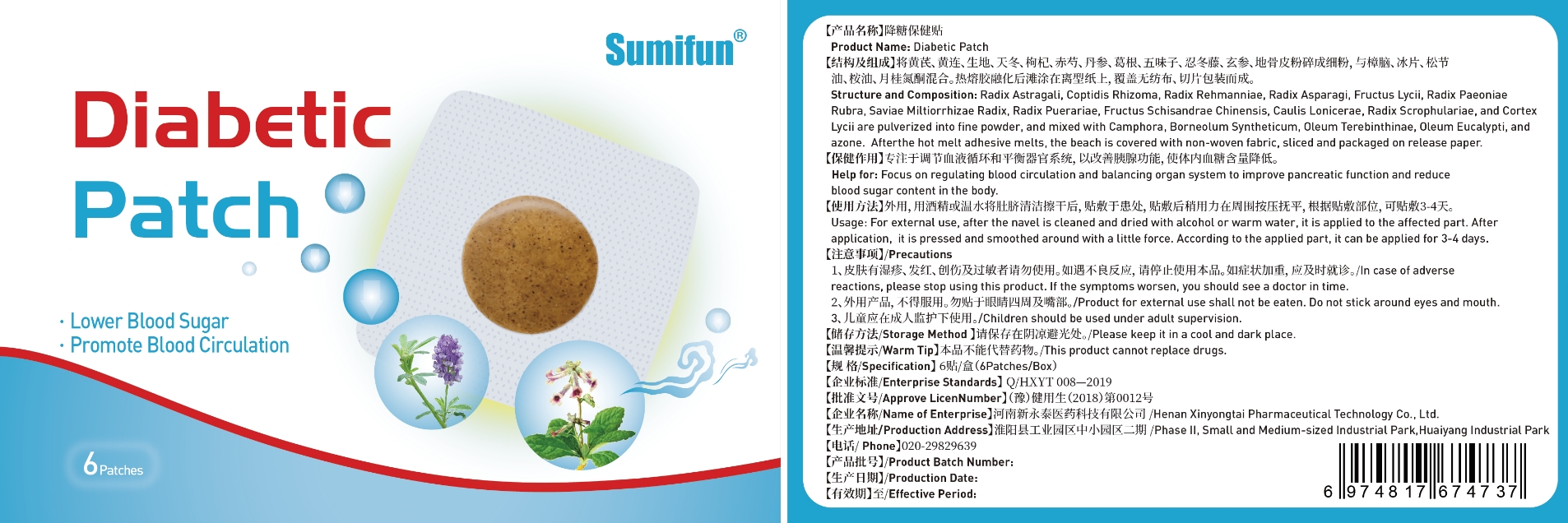 DRUG LABEL: Diabetic Patch
NDC: 83675-009 | Form: PATCH
Manufacturer: Guangzhou Hanhai Trading Co., Ltd
Category: otc | Type: HUMAN OTC DRUG LABEL
Date: 20230920

ACTIVE INGREDIENTS: ASTRAGALUS PROPINQUUS ROOT 13 g/100 1
INACTIVE INGREDIENTS: REHMANNIA GLUTINOSA ROOT; SALVIA MILTIORRHIZA ROOT; SARGENTODOXA CUNEATA WHOLE; LYCIUM BARBARUM FRUIT; ASPARAGUS COCHINCHINENSIS TUBER; RUBUS CHINGII WHOLE; PAEONIA LACTIFLORA ROOT; COPTIS TEETA ROOT; PUERARIA MONTANA VAR. LOBATA ROOT; SCROPHULARIA NINGPOENSIS ROOT

83675-009

Active Ingredient

Radix Astragali 13.0%

Purpose

Lower Blood Sugar

Use

Diabetic Patch to help lower blood sugar

Warnings

For external use only. Do not take it internally.

Keep Out Of Reach Of Children
Prohibited for those with damaged skin.

Do not use

Product shall not be eat

When Using

Do not stick around eyes and mouth,This product cannot replace drugs.

Stop Use

In case of adverse reactions, please stop using this product.If the symptoms.

Ask Doctor

ask doctor in case of adverse reactions

Keep Oot Of Reach Of Children

Keep Out Of Reach Of Children

Directions

Take one piece of this product when needed, remove the waxpaper,

stick to the desired area and press the surrounding, replace it every 3-4 days.

Children should be used under adult supervision.

Other information

Store the product in a cool, dry and well-ventilated place

Avoid direct sunlight

Inactive ingredients

Coptidis Rhizoma

Radix Rehmanniae

Radix Asparagi,

Fructus Lycii,

Radix Paeoniae Rubra,

Saviae Miltiorrhizae Radix,

Radix Puerariae,

Fructus Schisandrae Chinensis

Caulis Lonicerae

Radix Scrophulariae

Cortex Lycii